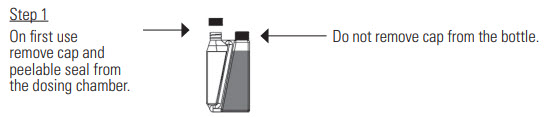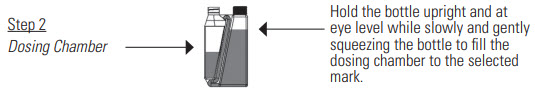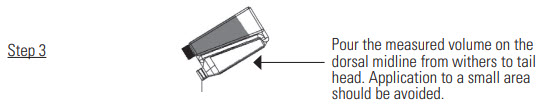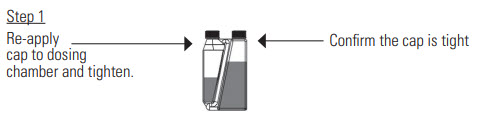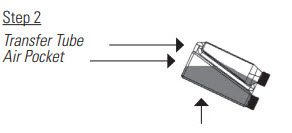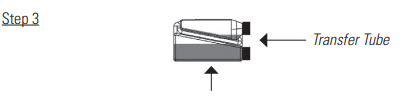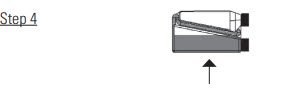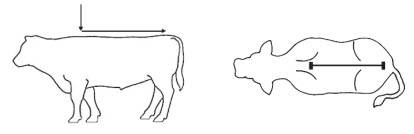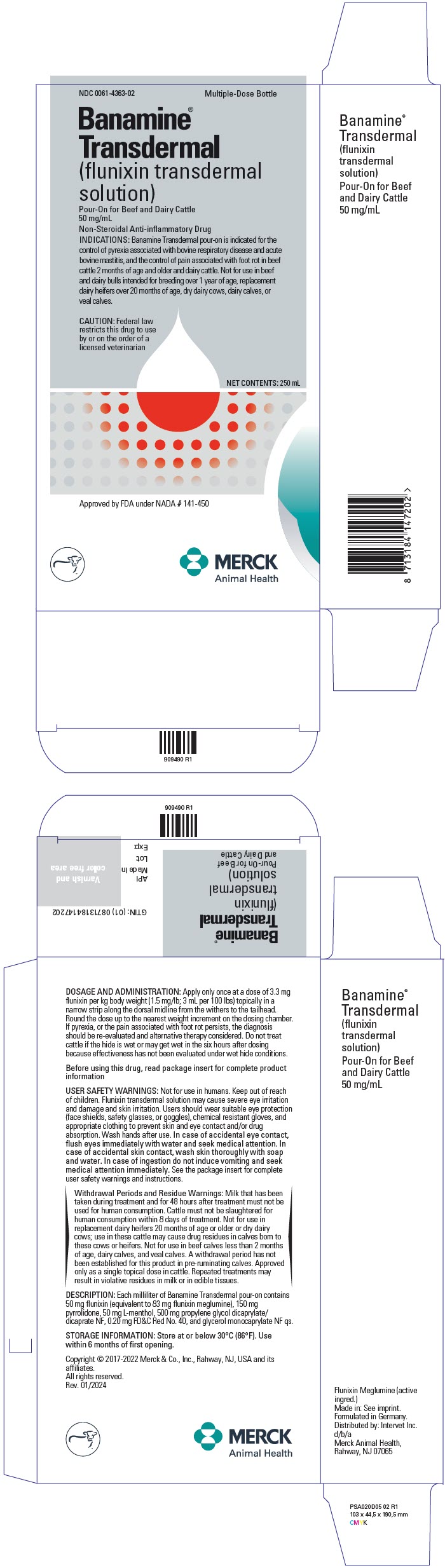 DRUG LABEL: Banamine
NDC: 0061-4363 | Form: SOLUTION
Manufacturer: Merck Sharp & Dohme Corp.
Category: animal | Type: PRESCRIPTION ANIMAL DRUG LABEL
Date: 20260219

ACTIVE INGREDIENTS: FLUNIXIN MEGLUMINE 50 mg/1 mL

Banamine® Transdermal
(flunixin transdermal solution)

Product Information

Approved by FDA under NADA # 141-450

Pour-On for Beef and Dairy Cattle
50 mg/mL

Non-Steroidal Anti-inflammatory Drug

CAUTION: Federal law restricts this drug to use by or on the order of a licensed veterinarian.

DESCRIPTION

DESCRIPTION: Each milliliter of Banamine Transdermal pour-on contains 50 mg flunixin (equivalent to 83 mg flunixin meglumine), 150 mg pyrrolidone, 50 mg L-menthol, 500 mg propylene glycol dicaprylate/dicaprate NF, 0.20 mg FD&C Red No. 40, and glycerol monocaprylate NF qs.

VETERINARY INDICATIONS

INDICATIONS: Banamine Transdermal pour-on is indicated for the control of pyrexia associated with bovine respiratory disease and acute bovine mastitis, and the control of pain associated with foot rot in beef cattle 2 months of age and older and dairy cattle.

Not for use in beef and dairy bulls intended for breeding over 1 year of age, replacement dairy heifers over 20 months of age, dry dairy cows, dairy calves, or veal calves.

DOSAGE AND ADMINISTRATION: Apply only once at a dose of 3.3 mg flunixin per kg body weight (1.5 mg/lb; 3 mL per 100 lbs) topically in a narrow strip along the dorsal midline from the withers to the tailhead. Round the dose up to the nearest weight increment on the dosing chamber. If pyrexia, or the pain associated with foot rot persists, the diagnosis should be re-evaluated and alternative therapy considered. Do not treat cattle if the hide is wet or may get wet in the six hours after dosing because effectiveness has not been evaluated under wet hide conditions.

Practice the Administration and Overfill Reduction Instructions a few times to become familiar with operating the package before dosing animals.

If the dosing chamber is overfilled follow the Overfill Reduction Instructions.

A small amount of liquid will remain on the walls of the chamber, but the chamber is calibrated to account for this.

OVERFILL REDUCTION INSTRUCTIONS

Tilt the bottle to allow an air pocket to form at the beginning of the transfer tube inside the bottle.

Hold the bottle horizontally to allow product to cover the end of the transfer tube inside the dosing chamber.

Squeeze and release the bottle repeatedly.
Product will return to the bottle through the transfer tube.

Figure 1 – Recommended pour-on location

CONTRAINDICATIONS

CONTRAINDICATIONS: NSAIDs inhibit production of prostaglandins which are important in signaling the initiation of parturition. The use of flunixin can delay parturition and prolong labor which may increase the risk of stillbirth. Do not use Banamine Transdermal pour-on within 48 hours of expected parturition. Do not use in animals showing hypersensitivity to flunixin meglumine.

SAFE HANDLING WARNING

USER SAFETY WARNINGS: Not for use in humans. Keep out of reach of children. Flunixin transdermal solution is a potent non-steroidal anti-inflammatory drug (NSAID), and ingestion may cause gastrointestinal irritation and bleeding, kidney, and central nervous system effects.

This product has been shown to cause severe and potentially irreversible eye damage (conjunctivitis, iritis, and corneal opacity) and irritation to skin in laboratory animals. Users should wear suitable eye protection (face shields, safety glasses, or goggles) to prevent eye contact; and chemical resistant gloves and appropriate clothing (such as long-sleeve shirt and pants) to prevent skin contact and/or drug absorption. Wash hands after use.

In case of accidental eye contact, flush eyes immediately with water and seek medical attention. If wearing contact lenses, flush eyes immediately with water before removing lenses. In case of accidental skin contact and/or clothing contamination, wash skin thoroughly with soap and water and launder clothing with detergent. In case of ingestion do not induce vomiting and seek medical attention immediately. Probable mucosal damage may contraindicate the use of gastric lavage. Provide product label and/or package insert to medical personnel.

Withdrawal Periods and Residue Warnings:

Milk that has been taken during treatment and for 48 hours after treatment must not be used for human consumption. Cattle must not be slaughtered for human consumption within 8 days of treatment. Not for use in replacement dairy heifers 20 months of age or older or dry dairy cows; use in these cattle may cause drug residues in calves born to these cows or heifers. Not for use in beef calves less than 2 months of age, dairy calves, and veal calves. A withdrawal period has not been established for this product in pre-ruminating calves. Approved only as a single topical dose in cattle. Repeated treatments may result in violative residues in milk or in edible tissues.

PRECAUTIONS

PRECAUTIONS: As a class, cyclo-oxygenase inhibitory NSAIDs may be associated with gastrointestinal, renal, and hepatic toxicity. Sensitivity to drug-associated adverse events varies with the individual patient. Patients at greatest risk for adverse events are those that are dehydrated, on concomitant diuretic therapy, or those with renal, cardiovascular, and/or hepatic dysfunction. Banamine Transdermal should be used with caution in animals with suspected pre-existing gastric erosions or ulcerations. Concurrent administration of other NSAIDs, corticosteroids, or potentially nephrotoxic drugs should be avoided or used only with careful monitoring because of the potential increase of adverse events. Banamine Transdermal is approved only as a single topical dose. The safety of repeated treatment has not been evaluated.

NSAIDs are known to have potential effects on both parturition (see Contraindications) and the estrous cycle. There may be a delay in the onset of estrus if flunixin is administered during the prostaglandin phase of the estrous cycle. NSAIDs are known to have the potential to delay parturition through a tocolytic effect. The use of NSAIDs in the immediate post-partum period may interfere with uterine involution and expulsion of fetal membranes. Cows should be monitored carefully for placental retention and metritis if Banamine Transdermal pour-on is used within 24 hours after parturition.

Not for use in beef and dairy bulls intended for breeding over 1 year of age because reproductive safety has not been evaluated.

CLINICAL PHARMACOLOGY

CLINICAL PHARMACOLOGY: Flunixin meglumine is a nonsteroidal, anti-inflammatory drug. It is a weak acid (pKa=5.82)^1 which exhibits a high degree of plasma protein binding (approximately 99%).^2 However, free (unbound) drug appears to readily partition into body tissues (Vss predictions range from 297 to 782 mL/kg).^2-5 In cattle, elimination occurs primarily through biliary excretion.

Flunixin persists in inflammatory tissues^6 and is associated with anti-inflammatory properties which extend well beyond the period associated with detectable plasma drug concentrations.^4,6 Therefore, prediction of drug concentrations based upon the estimated plasma terminal elimination half-life will likely underestimate both the duration of drug action and the concentration of drug remaining at the site of activity.

Pharmacokinetic properties of flunixin transdermal solution in cattle administered at a dose of 2.5 mg/kg, are summarized in Table 1, comparing results between animals that were allowed to self- and allo-lick vs. animals that were prevented from licking. Animals that were allowed to self- or allo-lick had lower rate and extent of absorption when compared to the animals prevented from licking. However, no dose adjustment is needed to account for the effect of licking because the substantial evidence of effectiveness was demonstrated in animals that were allowed to lick.

Table 1. Average (+/- standard deviation [SD]) PK parameters after a single administration of flunixin transdermal solution at a dose of 2.5 mg/kg in cattle that were either allowed to lick or prevented from allo- and self-licking (n = 24/group).
PK parameter | Non-licking |  | Licking
PK parameter | Mean | ± SD | Mean | ± SD
Cmax (ng/mL) | 1496 | 769 | N/A | N/A
Concentration at 2 h [First blood level in the licking group was taken at 2 hours post-dose. First blood sample in non-licking group was taken at 0.25 hours post-dose.] | 1282 | 533 | 1072 | 353
Tmax (h) | 1.29 | 0.464 | N/A | N/A
AUC2-last (ng*h/mL) | 7499 | 2131 | 6827 | 4672
T1/2 (h) | 8 | 2 | 9 | 6
Cmax: Maximum observed plasma concentration
Tmax: Time at which Cmax was observed
AUC2-last: Area under the plasma concentration versus time curve measured between 2 hours and the time of the last quantifiable concentration
T1/2: Terminal elimination half-life

Absorption of flunixin transdermal solution in cattle is dependent on environmental temperature. The effect of temperature on flunixin absorption was tested in temperatures ranging from 15.3 to 20.1 °F (average low in the coldest study) to 80 to 100 °F (average high in the warmest study). Flunixin concentrations were consistently lower when the pour-on product was administered in a cold (temperature) rather than hot (temperature) environment. However, the clinical effectiveness was demonstrated over the range of environmental conditions expected under field conditions. No dose adjustments are necessary due to environmental temperature.

References:

1. Johansson M, Anler EL. Gas chromatographic analysis of flunixin in equine urine after extractive methylation. J Chromatogr. 1988; 427:55-66.

2. Odensvik K, Johansson M. High-performance liquid chromatography method for determination of flunixin in bovine plasma and pharmacokinetics after single and repeated doses of the drug. Am J Vet Res. 1995; 56:489-495.

3. Anderson KL, Neff-Davis CA, Davis LE, Bass VD. Pharmacokinetics of flunixin meglumine in lactating cattle after single and multiple intramuscular and intravenous administrations. Am J Vet Res. 1990; 51:1464-1467.

4. Odensvik K. Pharmacokinetics of flunixin and its effect on prostaglandin F2α metabolite concentrations after oral and intravenous administration in heifers. J Vet Pharmacol Ther. 1995;18:254-259.

5. Hardee GE, Smith JA, Harris SJ. Pharmacokinetics of flunixin meglumine in the cow. Res Vet Sci. 1985; 39:110-112.

6. Lees P, Higgins AJ. Flunixin inhibits prostaglandin E2 production in equine inflammation. Res Vet Sci. 1984; 37:347-349.

TARGET ANIMAL SAFETY: In a target animal safety study in 32 six-month old beef cattle (16 castrated males and 16 females), flunixin transdermal solution was administered topically at 3.3, 9.9, and 16.5 mg/kg body weight (1× , 3× , and 5× the labeled dose) on Days 1, 2, and 3 (3× the labeled administration frequency). Cattle were continuously restrained to prevent licking. In addition, the study was conducted under warm environmental conditions (70 °F to 80 °F on dosing days). One animal in the 3× group and three animals in the 5× group exhibiting twisting, kicking, rubbing on the fence, and or prancing, starting 5 to 15 minutes after dosing and lasting up to an hour after dosing on both Days 2 and 3. Two 5× animals had positive fecal occult blood on one of three post-treatment days, and one 5× animal had positive fecal occult blood on Days 2 and 3 post-treatment. Trace occult blood was found in the urine of three animals: one 5× animal on Day 1, one 5× animal on Day 3, and one 3× animal on Day 3. Test article-related pathology changes included a dose-related increase in the incidence and severity of abomasal erosions and ulcerations; and inflammatory cell infiltrates, epidermal necrosis, and small areas of dermal necrosis at the application site. The abomasal lesions correlated with fecal occult blood in three 5× animals. There were no animals with any other evidence of gastrointestinal bleeding or clinical signs of abomasal ulceration during the study.

Application site reactions, including dandruff/skin flakes, hair damage (thin, broken, brittle hair), and skin thickening were observed in effectiveness and/or supportive studies. The application site reactions were first observed around three to seven days post-dosing and lasted for about 14 days. These reactions were cosmetic in nature and generally resolved without treatment.

A pharmacokinetic evaluation demonstrated that the systemic exposure of flunixin is markedly lower when administered transdermally at a dose of 3.3 mg flunixin/ kg BW than when administered intravenously at a dose of 2.2 mg flunixin/kg BW, therefore, female reproductive safety is supported by reproductive safety studies conducted for the approval of BANAMINE (flunixin meglumine injection) in cattle, NADA 101-479.

EFFECTIVENESS:

Clinical field studies – bovine respiratory disease

Pharmacokinetic studies established that the absorption of flunixin administered transdermally to cattle is highly dependent on environmental temperature. Therefore the effectiveness of flunixin transdermal solution for the control of pyrexia associated with bovine respiratory disease was demonstrated under a range of environmental temperatures in two studies: a field study conducted at four geographic locations (California, Kansas, Nebraska, and Texas) under moderate environmental temperatures (average temperatures ranged from 42 °F to 74 °F on enrollment days) and a field study conducted at a single site (Nebraska) under cold environmental conditions (average temperatures ranged from 2 °F to 20 °F on enrollment days). In both studies, cattle were housed in groups and were not prevented from licking.

In both studies, cattle exhibiting clinical signs of BRD and having a rectal temperature of at least 104.5 °F were enrolled. A total of 235 cattle in the multi-location field study and 50 cattle at the single site field study were administered either flunixin transdermal solution (3.3 mg/kg BW) or an equivalent volume of dyed saline as a pour-on once on Day 0. Six hours after treatment, rectal temperatures were measured. The treatment success rate of the flunixin transdermal solution-treated group was compared to the treatment success rate in the dyed saline control group. A treatment success was defined as a drop in rectal temperature of ≥ 2 °F in an individual animal. In the multi-location study, the treatment success rate was significantly different (p < 0.0001) and higher for the flunixin transdermal solution-treated group (70/120, 58.3%) compared to the dyed saline control group (7/115, 6.1%). In the single site study, the treatment success rate was significantly different (p = 0.0002) and higher for the flunixin transdermal solution- treated group (19/25, 76%) compared to the dyed saline control group (4/25, 16%).

Induced infection model studies – foot rot

The effectiveness of flunixin transdermal solution for the control of pain associated with foot rot in beef and dairy cattle was demonstrated under a range of environmental temperatures in two studies: an induced infection model study conducted in Nebraska with temperatures ranging from 61 °F to 85 °F on the day of enrollment and treatment; and an induced infection model study conducted in Kansas with temperatures ranging from 27 °F to 53 °F on the day of enrollment and treatment. In both studies, cattle from both treatment groups were commingled in pens and were not prevented from licking.

In each study, cattle were challenged by subcutaneous injection of a culture of Fusobacterium necrophorum into the interdigital space of the right front foot using a method that was validated to induce pain representative of foot rot.

Cattle were enrolled when they demonstrated signs of pain associated with foot rot based on lameness, interdigital lesion, and interdigital swelling criteria. Pressure mat gait parameters maximum total force (kgf) and contact area (cm^2) were also measured at enrollment. A total of 30 cattle at each site were administered either flunixin transdermal solution (3.3 mg/kg BW) or an equivalent volume of dyed saline as a pour-on once on Day 0. Six hours after treatment, lameness scores and pressure mat gait parameters maximum total force and contact area were measured.

Effectiveness was determined independently at each site based on treatment success rates at six hours after treatment; and the change in maximum total force and contact area between enrollment and six hours after treatment. A treatment success was defined as a decrease in lameness score by ≥ 1 (scale 1 to 5, with enrollment of animals with lameness score ≥ 3) from the enrollment lameness score. The treatment success rate of the flunixin transdermal solution-treated group was compared to the treatment success rate in the dyed saline control group at both sites.

Changes in biometric gait parameters were also compared between the treatment groups.

In the Nebraska study, the treatment success rate was significantly different and higher for the flunixin transdermal solution-treated group (15/15, 100%) compared to the dyed saline control group (1/15, 6.67%); and the mean change in maximum total force and mean change in contact area were statistically significantly different (p <0.0001) and higher in the flunixin transdermal solution-treated group (43.08 kgf and 16.76 cm^2) compared to the dyed saline control group (-4.14 kgf and -2.70 cm^2). In the Kansas study, the treatment success rate was significantly different (p=0.0387) and higher for the flunixin transdermal solution-treated group (14/15, 93.33%) compared to the dyed saline control group (8/15, 53.33%); and the mean change in maximum total force and mean change in contact area were statistically significantly different (p= 0.0002 and p<0.0001, respectively) and higher in the flunixin transdermal solution-treated group (34.32 kgf and 16.38 cm^2) compared to the dyed saline control group (-0.54 kgf and -0.96 cm^2).

Clinical field study – acute bovine mastitis

The effectiveness of flunixin transdermal solution for the control of pyrexia associated with acute bovine mastitis was demonstrated under a range of environmental temperatures (37.4 °F to 86 °F) in a multi-site field study conducted in France, Germany, and Spain. Cattle were housed in a manner which did not prevent them from licking themselves or other cows. Lactating dairy cows were enrolled when they exhibited acute signs of mastitis in one or two quarters (based on an evaluation of udder firmness, swelling, and pain), milk characteristics consistent with mastitis, and a rectal temperature of at least 104 °F.

Enrolled cows were administered either flunixin transdermal solution (3.3 mg flunixin/kg BW) or an equivalent volume of dyed saline as a pour-on once on Day 0. Six hours after treatment, rectal temperatures were measured. The treatment success rate of the flunixin transdermal solution-treated group was compared to the treatment success rate in the dyed saline control group. A treatment success was defined as a drop in rectal temperature of ≥ 2 °F in an individual animal. The treatment success rate was significantly different (p < 0.0001) and higher in the flunixin transdermal solution-treated group (61/64, 95%) compared to the dyed saline control group (23/66, 35%).

CONTACT INFORMATION:

For technical assistance or to report a suspected adverse drug experience, call: 1-800-211-3573

For customer service or to request a Safety Data Sheet (SDS), call: 1-800-521-5767

For additional Banamine Transdermal pour-on information go to www.BanamineTD.com

For additional information about adverse drug experience reporting for animal drugs, contact FDA at 1-888-FDA-VETS or online at www.fda.gov/reportanimalae

HOW SUPPLIED

HOW SUPPLIED: Banamine Transdermal pour-on, is available in 100-mL (NDC 0061-4363-01), 250-mL (NDC 0061-4363-02), and 1-L (NDC 0061-4363-03) bottles.

STORAGE AND HANDLING

STORAGE INFORMATION: Store at or below 30°C (86°F). Use within 6 months of first opening.

For Patent information: http://www.merck.com/product/patent/home.html
Approved by FDA under NADA # 141-450
Use Only as Directed
Copyright © 2017-2022 Merck & Co., Inc., Rahway, NJ, USA and its affiliates.
All rights reserved.
Formulated in Germany
Distributed by: Intervet Inc. d/b/a Merck Animal Health, Rahway, NJ 07065

Rev. 01/2024

PRINCIPAL DISPLAY PANEL - 250 mL Bottle Carton

NDC 0061-4363-02
Multiple-Dose Bottle

Banamine®
Transdermal
(flunixin transdermal
solution)

Pour-On for Beef and Dairy Cattle
50 mg/mL

Non-Steroidal Anti-inflammatory Drug

INDICATIONS: Banamine Transdermal pour-on is indicated for the
control of pyrexia associated with bovine respiratory disease and acute
bovine mastitis, and the control of pain associated with foot rot in beef
cattle 2 months of age and older and dairy cattle. Not for use in beef
and dairy bulls intended for breeding over 1 year of age, replacement
dairy heifers over 20 months of age, dry dairy cows, dairy calves, or
veal calves.

CAUTION: Federal law
restricts this drug to use
by or on the order of a
licensed veterinarian

NET CONTENTS: 250 mL

Approved by FDA under NADA # 141-450

MERCK
Animal Health